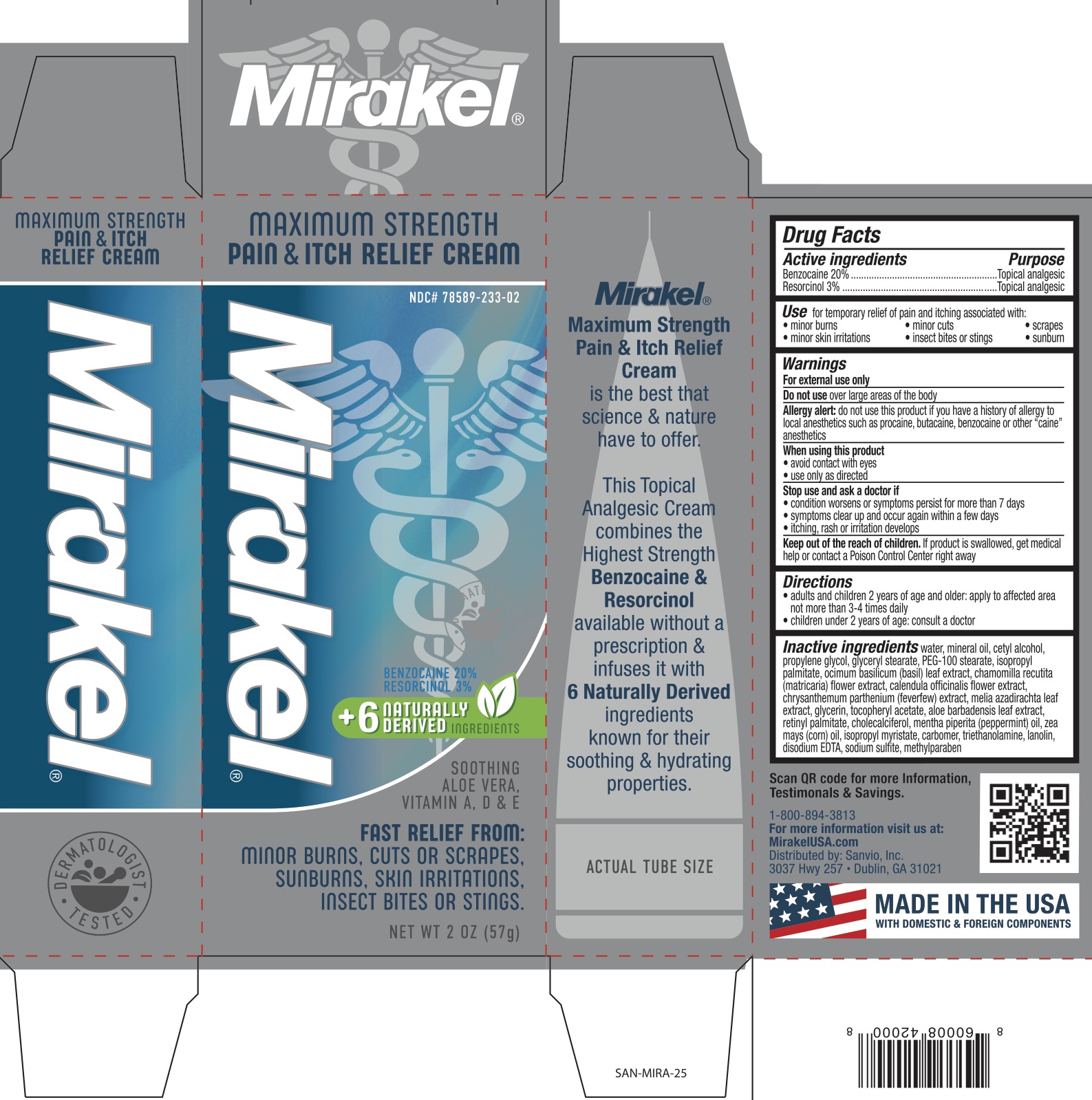 DRUG LABEL: Mirakel Pain and Itch Relief
NDC: 78589-233 | Form: CREAM
Manufacturer: Sanvio, Inc.
Category: otc | Type: HUMAN OTC DRUG LABEL
Date: 20241220

ACTIVE INGREDIENTS: BENZOCAINE 20 g/100 g; RESORCINOL 3 g/100 g
INACTIVE INGREDIENTS: ISOPROPYL MYRISTATE; VITAMIN A PALMITATE; GLYCERYL MONOSTEARATE; ALOE VERA LEAF; CETYL ALCOHOL; WATER; GLYCERIN; CALENDULA OFFICINALIS FLOWER; CHAMOMILE; .ALPHA.-TOCOPHEROL ACETATE; BASIL; METHYLPARABEN; CARBOMER 934; PROPYLENE GLYCOL; PEG-100 STEARATE; FEVERFEW; AZADIRACHTA INDICA LEAF; EDETATE DISODIUM; MINERAL OIL; CHOLECALCIFEROL; PEPPERMINT OIL; CORN OIL; TROLAMINE; LANOLIN; SODIUM SULFITE

Mirakel Max Strength Pain and Itch Relief, Benzocaine 20%, Resorcinol 3%

ACTIVE INGREDIENT

Benzocaine 20%, Resorcinol 3%

PURPOSE

Topical analgesic

INDICATIONS AND USAGE

For the temporary relief of minor aches and pain associated with minor burns, minor skin irritations, minor cuts, insect bites or stings, scrapes, and sunburns.

WARNINGS

For external use only. Do not use over large areas of the body. Allergy alert: do not use this product if you have a history of allergy to local anesthetics such as procaine, butacaine, benzocaine, or other "caine" anesthetics. When using this product avoid contact with eyes, use only as directed. Stop use and ask a doctor if condition worsens, if symptoms persist for more than 7 days, symptoms clear up and occur again within a few days, itching, rash or irritation develops.

KEEP OUT OF REACH OF CHILDREN

If swallowed, get medical help or contact a Poison Control Center right away.

DOSAGE AND ADMINISTRATION

Adults and children 2 years of age and older, apply to the affected area not more than 3 to 4 times daily. Children under 2 years of age: ask a doctor.

INACTIVE INGREDIENT

Water, mineral oil, cetyl alcohol, propylene glycol, glyceryl stearate, PEG-100 stearate, isopropyl palmitate, ocimum basilicum (basil) leaf extract, chamomilla recutita (matricaria) flower extract, calendula officinalis flower extract, chrysanthemum parthenium (feverfew) extract, melia azadirachta leaf extract, glycerin, tocopheryl acetate, aloe barbadensis leaf extract, retinyl palmitate, cholecalciferol, mentha piperita (peppermint) oil, zea mays (corn) oil, isopropyl myristate, carbomer, triethanolamine, lanolin, disodium EDTA, sodium sulfite, methylparaben.